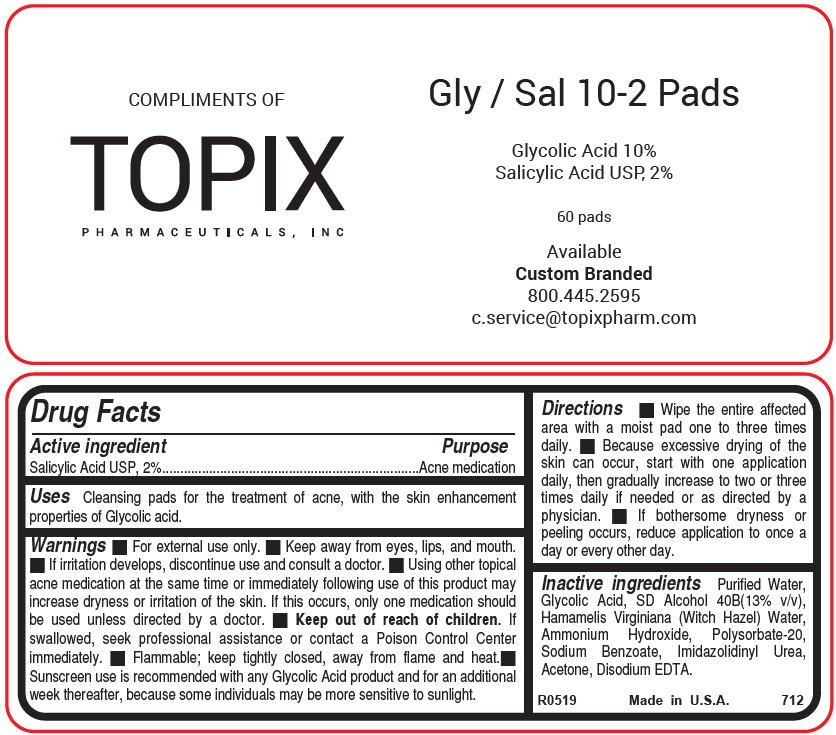 DRUG LABEL: Gly-Sal 10-2
NDC: 51326-712 | Form: CLOTH
Manufacturer: Topiderm, Inc.
Category: otc | Type: HUMAN OTC DRUG LABEL
Date: 20250602

ACTIVE INGREDIENTS: SALICYLIC ACID 20 mg/1 1
INACTIVE INGREDIENTS: WATER; GLYCOLIC ACID 100 mg/1 1; ALCOHOL 95% 130 mL/1 1; HAMAMELIS VIRGINIANA LEAF WATER; AMMONIA; POLYSORBATE 20; SODIUM BENZOATE; IMIDUREA; ACETONE; EDETATE DISODIUM

Gly-Sal 10-2

Drug Facts

Active ingredient

Salicylic Acid USP, 2%

Purpose

Acne medication

Uses

Cleansing pads for the treatment of acne, with the skin enhancement properties of Glycolic acid.

Warnings

- For external use only.
- Keep away from eyes, lips, and mouth.
- If irritation develops, discontinue use and consult a doctor.
- Using other topical acne medication at the same time or immediately following use of this product may increase dryness or irritation of the skin. If this occurs, only one medication should be used unless directed by a doctor.

- Keep out of reach of children. If swallowed, seek professional assistance or contact a Poison Control Center immediately.
- Flammable; keep tightly closed, away from flame and heat.
- Sunscreen use is recommended with any Glycolic Acid product and for an additional week thereafter, because some individuals may be more sensitive to sunlight.

Directions

- Wipe the entire affected area with a moist pad one to three times daily.
- Because excessive drying of the skin can occur, start with one application daily, then gradually increase to two or three times daily if needed or as directed by a physician.
- If bothersome dryness or peeling occurs, reduce application to once a day or every other day.

Inactive ingredients

Purified Water, Glycolic Acid, SD Alcohol 40B(13% v/v), Hamamelis Virginiana (Witch Hazel) Water, Ammonium Hydroxide, Polysorbate-20, Sodium Benzoate, Imidazolidinyl Urea, Acetone, Disodium EDTA.

PRINCIPAL DISPLAY PANEL - 60 Pad Jar

COMPLIMENTS OF
TOPIX
PHARMACEUTICALS, INC

Gly / Sal 10-2 Pads

Glycolic Acid 10%
Salicylic Acid USP, 2%

60 pads

Available
Custom Branded
800.445.2595
c.service@topixpharm.com